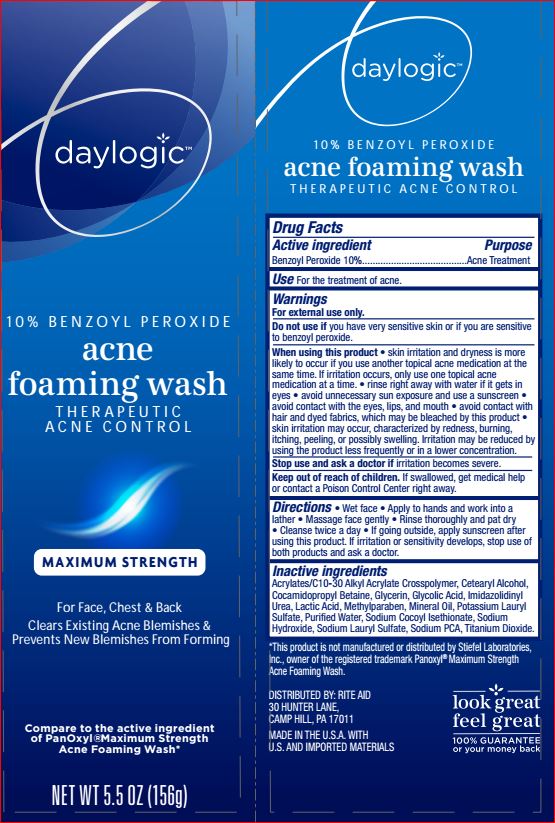 DRUG LABEL: Acne Foaming Wash
NDC: 11822-1216 | Form: CREAM
Manufacturer: Rite Aid
Category: otc | Type: HUMAN OTC DRUG LABEL
Date: 20180514

ACTIVE INGREDIENTS: BENZOYL PEROXIDE 10 g/100 g
INACTIVE INGREDIENTS: CARBOMER COPOLYMER TYPE B (ALLYL PENTAERYTHRITOL CROSSLINKED); CETOSTEARYL ALCOHOL; COCAMIDOPROPYL BETAINE; GLYCERIN; GLYCOLIC ACID; IMIDUREA; LACTIC ACID; METHYLPARABEN; MINERAL OIL; POTASSIUM LAURYL PHOSPHATE; WATER; SODIUM COCOYL ISETHIONATE; SODIUM HYDROXIDE; SODIUM LAURYL SULFATE; SODIUM PYRROLIDONE CARBOXYLATE; TITANIUM DIOXIDE

Drug Facts

Active ingredient

Benzoyl Peroxide 10%

Purpose

Acne Treatment

Uses

For the treatment of acne.

Warnings

For external use only

Do not use if

you have very sensitive skin or if you are sensitive to benzoyl peroxide

When using this product

- skin irritation and dryness is more likely to occur if you use another topical acne medication at the same time
- if irritation occurses, only use one topical acne medicine at the time
- rinse rightaway with water if it gets in eyes
- avoid unnecessary sun exposure and use a sunscreen
- avoid contact with the eyes, lips, and mouth
- avoid contact with hair and dyed fabrics, which may be bleached by this product
- skin irritation may occurs, characterized by redness, burning, itching, peeling, or possibly swelling. Irritation may be reduced by using the product less frequently or in a low concentration.

Stop use and consult a doctor if

irritation become severe.

Keep out of reach of children

If swallowed, get medical help or contact a Poison Control Center right away

Directions

- Wet face
- Apply to hands and work into a lather
- Massage face gently
- Rinse thoroughly and pat dry
- Clease twice a day
- If going outside apply sunscreen after using this product. If irritation or sensitivity develops, stop use of both products and consult a doctor

Inactive ingredients

Acrylates/C10-30 Alkyl Acrylate Crosspolymer, Cetearyl Alcohol, Cocamidopropyl Betaine, Glycerin, Glycolic Acid, Imidazolidinyl Urea, Lactic Acid, Methylparaben, Mineral Oil, Potassium lauryl Sulfate, Purified Water, Sodium Cocoyl Isethionate, Sodium Hydroxide, Sodium Lauryl Sulfate, Sodium PCA, Titanium Dioxide